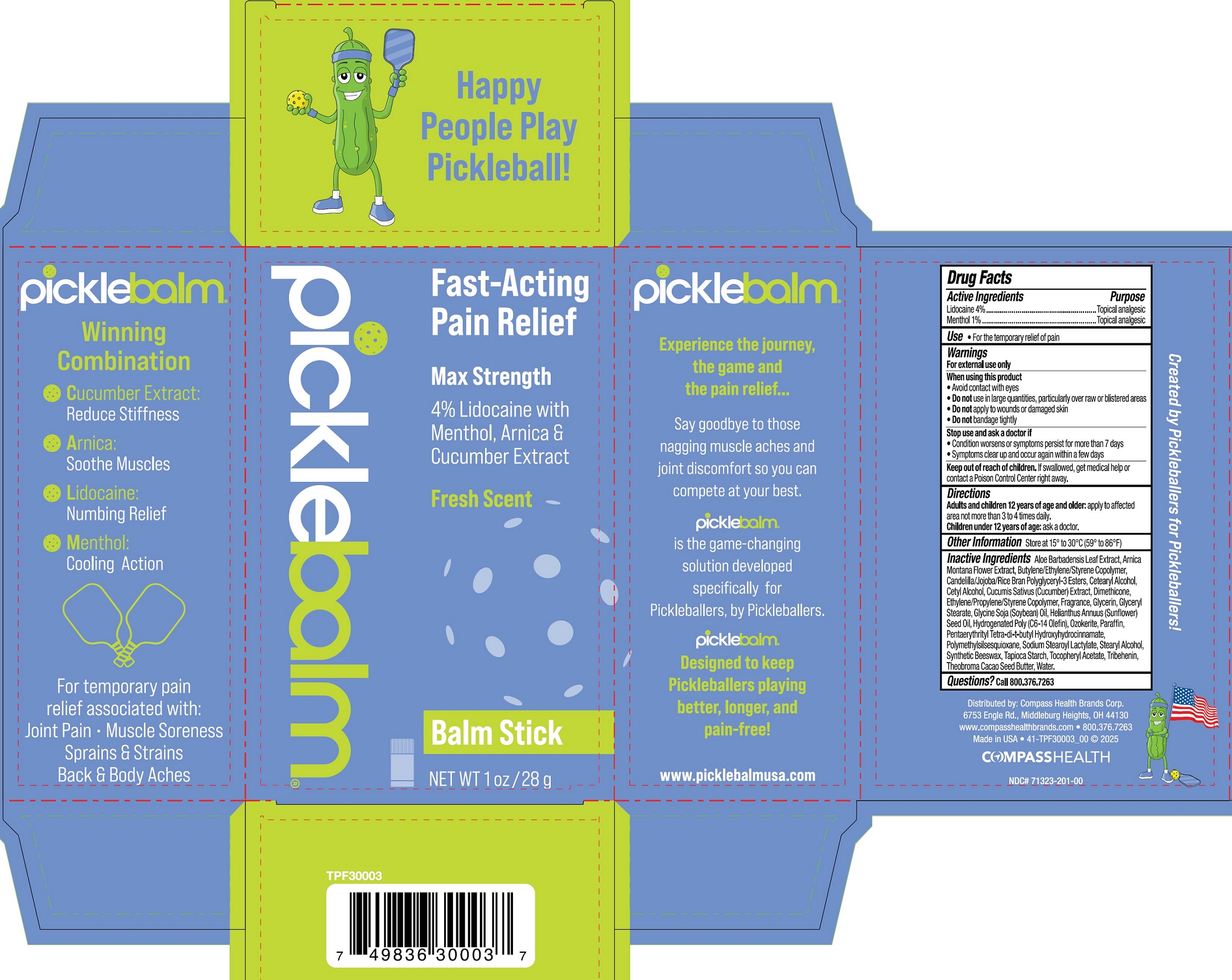 DRUG LABEL: PICKLEBALM LIDOCAINE WITH MENTHOL ARNICA CUCUMBER SEED BALM
NDC: 71323-201 | Form: STICK
Manufacturer: Compass Health Brands Corp.
Category: otc | Type: HUMAN OTC DRUG LABEL
Date: 20250422

ACTIVE INGREDIENTS: LIDOCAINE 40 mg/1 g; MENTHOL, UNSPECIFIED FORM 10 mg/1 g
INACTIVE INGREDIENTS: ALOE VERA LEAF JUICE; ARNICA MONTANA FLOWER; CETOSTEARYL ALCOHOL; CETYL ALCOHOL; CUCUMBER; DIMETHICONE; GLYCERIN; SOYBEAN OIL; SUNFLOWER OIL; PARAFFIN; PENTAERYTHRITOL TETRAKIS(3-(3,5-DI-TERT-BUTYL-4-HYDROXYPHENYL)PROPIONATE); SODIUM STEAROYL LACTYLATE; STEARYL ALCOHOL; SYNTHETIC BEESWAX; TAPIOCA STARCH; .ALPHA.-TOCOPHEROL ACETATE; TRIBEHENIN; WATER

PICKLEBALM LIDOCAINE WITH MENTHOL ARNICA CUCUMBER SEED BALM STICK

Active Ingredients

Lidocaine 4%

Menthol 1%

Purpose

Topical analgesic

Use

- For the temporary relief of pain

Warnings

For external use only

When using this product

- Avoid contact with eyes
- Do notuse in large quantities, particularly over raw or blistered areas
- Do notapply to wounds or damaged skin
- Do notbandage tightly

Stop use and ask a doctor if

- Condition worsens or symptoms persist for more than 7 days
- Symptoms clear up and occur again within a few days

Keep out of reach of children.

If swallowed, get medical help or contact a Poison Control Center right away.

Directions

Adults and children 12 years of age and older:apply to affected area not more than 3 to 4 times daily.

Children under 12 years of age: ask a doctor.

Other Information

- Store at 15° to 30°C (59° to 86°F)

Inactive Ingredients

Aloe Barbadensis Leaf Juice, Arnica Montana Flower Extract, Butylene/Ethylene/Styrene Copolymer, Candelilla/Jojoba/Rice Bran Polyglyceryl-3 Esters, Cetearyl Alcohol, Cetyl Alcohol, Cucumis Sativa (Cucumber) Extract, Dimethicone, Ethylene/Propylene/Styrene Copolymer, Fragrance, Glycerin, Glyceryl Sterate, Glycine Soja (Soybean) Oil, Helianthus Annuus (Sunflower) Seed Oil, Hydrogenated poly (C6-14 Olefin), Ozokerite, Paraffin, Pentaerythrityl Tetra-di-t-butyl Hydroxyhydrocinnamate, Polymethylsilsesquioxane, Sodium Stearoyl Lactylate, Stearyl Alcohol, Synthetic Beeswax, Tapioca Starch, Tocopheryl Acetate, Tribehenin, Theobroma Cacao Seed Butter, Water.

Questions?

Call 800.376.7263